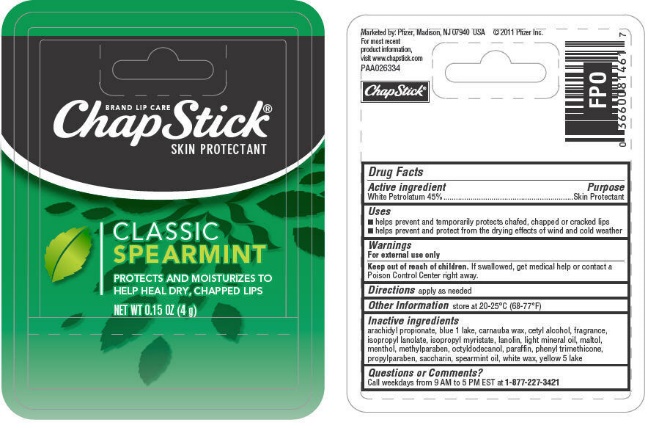 DRUG LABEL: ChapStick Classic Spearmint
NDC: 0573-1912 | Form: STICK
Manufacturer: Haleon US Holdings LLC
Category: otc | Type: HUMAN OTC DRUG LABEL
Date: 20240412

ACTIVE INGREDIENTS: PETROLATUM 450 mg/1 g
INACTIVE INGREDIENTS: ARACHIDYL PROPIONATE; FD&C BLUE NO. 1; CARNAUBA WAX; CETYL ALCOHOL; ISOPROPYL MYRISTATE; LANOLIN; LIGHT MINERAL OIL; MALTOL; LEVOMENTHOL; METHYLPARABEN; OCTYLDODECANOL; PARAFFIN; PHENYL TRIMETHICONE; PROPYLPARABEN; SACCHARIN; SPEARMINT OIL; WHITE WAX; FD&C YELLOW NO. 5

Drug Facts

Active ingredient

White Petrolatum 45%

Purpose

Skin Protectant

Uses

- helps prevent and temporarily protects chafed, chapped or cracked lips
- helps prevent and protect from the drying effects of wind and cold weather

Warnings

For external use only

Keep out of reach of children.If swallowed, get medical help or contact a Poison Control Center right away.

Directions

apply as needed

Other information

store at 20-25°C (68-77°F)

Inactive ingredients

arachidyl propionate, blue 1 lake, carnauba wax, cetyl alcohol, fragrance, isopropyl lanolate, isopropyl myristate, lanolin, light mineral oil, maltol, menthol, methylparaben, octyldodecanol, paraffin, phenyl trimethicone, propylparaben, saccharin, spearmint oil, white wax, yellow 5 lake

Questions or Comments?

Call weekdays from 9 AM to 5 PM EST at 1-877-227-3421

For most recent product information, visit www.chapstick.com

PRINCIPAL DISPLAY PANEL - 4 g Cylinder Blister Pack

BRAND LIP CARE
ChapStick®
SKIN PROTECTANT

CLASSIC
SPEARMINT

PROTECTS AND MOISTURIZES TO
HELP HEAL DRY, CHAPPED LIPS

NET WT 0.15 OZ (4 g)